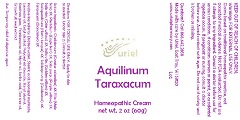 DRUG LABEL: Aquilinum Taraxacum
NDC: 48951-1311 | Form: CREAM
Manufacturer: Uriel Pharmacy Inc.
Category: homeopathic | Type: HUMAN OTC DRUG LABEL
Date: 20181116

ACTIVE INGREDIENTS: TARAXACUM PALUSTRE ROOT 3 [hp_X]/1 g; ASPLENIUM SCOLOPENDRIUM TOP 3 [hp_X]/1 g; WILLOW BARK 3 [hp_X]/1 g; DRYOPTERIS FILIX-MAS ROOT 3 [hp_X]/1 g; SOLIDAGO CANADENSIS FLOWERING TOP 3 [hp_X]/1 g; PTERIDIUM AQUILINUM WHOLE 3 [hp_X]/1 g; CHELIDONIUM MAJUS 3 [hp_X]/1 g; SALIX PURPUREA BARK 3 [hp_X]/1 g; SALIX ALBA FLOWER 3 [hp_X]/1 g
INACTIVE INGREDIENTS: XANTHAN GUM; POLYOXYL 40 STEARATE; TEA TREE OIL; CITRUS PARADISI SEED; FRANKINCENSE OIL; WATER; STEARIC ACID; ISOPROPYL MYRISTATE; LAVENDER OIL; MYRRH OIL; CETYL ALCOHOL; STEARYL ALCOHOL; SORBIC ACID

Aquilinum Taraxacum

INDICATIONS AND USAGE

Directions: FOR TOPICAL USE ONLY.

DOSAGE AND ADMINISTRATION

Apply to skin as needed. Under age 2: Consult a doctor.

ACTIVE INGREDIENT

Active Ingredients: Chelidonium (Greater celandine) 3X, Filix (Male fern) 3X, Pteridium (Eagle fern) 3X, Salix purp. (Purple willow) 3X, Salix vim. (Osier willow) 3X, Salix vite. (Golden willow) 3X, Scolopendrium (Hart’s tongue) 3X, Solidago virg. (Goldenrod) 3X, Taraxacum (Dandelion) 3X

INACTIVE INGREDIENT

Inactive Ingredients: Distilled water, Stearic acid, Isopropyl myristate, Lavender oil, Cetyl alcohol, Polyoxyl 40 stearate, Steryl alcohol, Xanthan gum, Frankincense oil, Myrrh oil, Sorbic acid, Tea tree oil, Grapefruit seed extract

PURPOSE

Use: Temporary relief of digestive upset.

KEEP OUT OF REACH OF CHILDREN.

Warnings: FOR EXTERNAL USE ONLY.
Claims based on traditional homeopathic practice, not accepted medical evidence. Not FDA evaluated. Do not use if allergic to any ingredient. Consult a doctor before use for serious conditions, if conditions worsen or persist, or accidental ingestion occurs. If pregnant or nursing, consult a doctor before use. Avoid contact with eyes. Do not use if safety seal is broken or missing.

Questions? Call 866.642.2858
Made with care by Uriel, East Troy, WI 53120
www.urielpharmacy.com